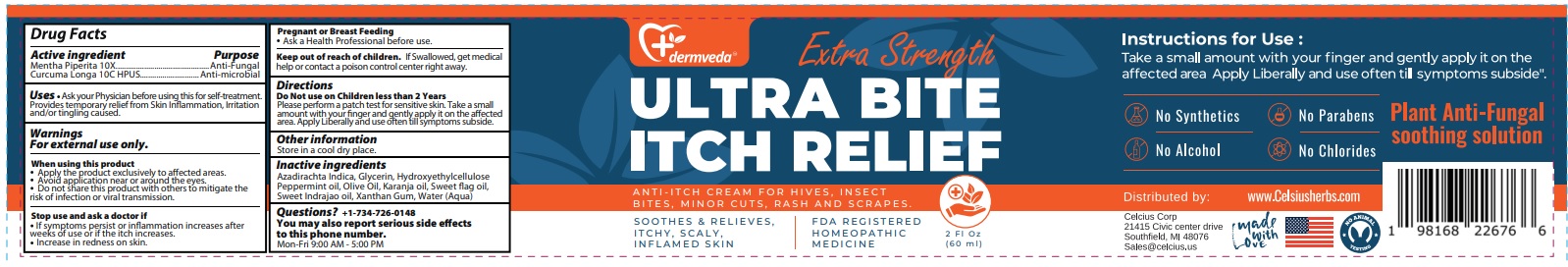 DRUG LABEL: Dermveda ULTRA BITE ITCH RELIEF
NDC: 83819-106 | Form: CREAM
Manufacturer: Celcius Corp.
Category: homeopathic | Type: HUMAN OTC DRUG LABEL
Date: 20260216

ACTIVE INGREDIENTS: MENTHA X PIPERITA WHOLE 10 [hp_X]/60 mL; TURMERIC 10 [hp_C]/60 mL
INACTIVE INGREDIENTS: AZADIRACHTA INDICA BARK; GLYCERIN; HYDROXYETHYL CELLULOSE, UNSPECIFIED; PEPPERMINT OIL; OLIVE OIL; KARUM SEED OIL; CALAMUS OIL; WRIGHTIA TINCTORIA WHOLE; XANTHAN GUM; WATER

Dermveda ULTRA BITE ITCH RELIEF

Active ingredient

Mentha Piperita 10X
Curcuma Longa 10C HPUS

Purpose

Anti-Fungal
Anti-microbial

Uses

• Ask your Physician before using this for self-treatment. Provides temporary relief from Skin Inflammation, Irritation and/or tingling caused.

Warnings

For external use only.

When using this product
• Apply the product exclusively to affected areas.
• Avoid application near or around the eyes.
• Do not share this product with others to mitigate the risk of infection or viral transmission.

Stop use and ask a doctor if
• If symptoms persist or inflammation increases after weeks of use or if the itch increases.
• Increase in redness on skin.

Pregnant or Breast Feeding
• Ask a Health Professional before use.

Keep out of reach of children. If swallowed, get medical help or contact a poison control center right away.

Directions

Do Not use on Children less than 2 Years
Please perform a patch test for sensitive skin. Take a small amount with your finger and gently apply it on the affected area. Apply Liberally and use often till symptoms subside.

Other information

Store in a cool dry place.

Inactive ingredients

Azadirachta Indica, Glycerin, Hydroxyethylcellulose, Peppermint oil, Olive Oil, Karanja oil, Sweet flag oil, Sweet Indrajao oil, Xanthan Gum, Water (Aqua)

Questions?

+1-734-726-0148
You may also report serious side effects to this phone number

Mon-Fri 9:00 AM - 5:00 PM

dermveda™

Extra Strength

ANTI-ITCH CREAM FOR HIVES, INSECT BITES, MINOR CUTS, RASH AND SCRAPES.

SOOTHES & RELIEVES, ITCHY, SCALY, INFLAMED SKIN

FDA REGISTERED HOMEOPATHIC MEDICINE

Instructions for Use: Take a small amount with your finger and gently apply it on the affected area. Apply Liberally and use often till symptoms subside.

No Synthetics

No Parabens

No Alcohol

No Chlorides

Plant Anti-Fungal soothing solution

Distributed by:

Celcius Corp
21415 Civic center drive
Southfield, MI 48076
Sales@celcius.us

made with Love

www.Celsiusherbs.com

NO ANIMAL TESTING